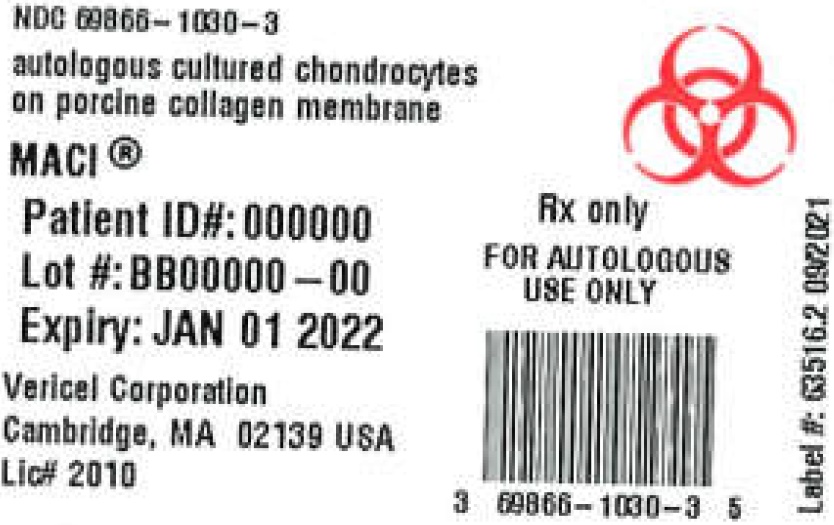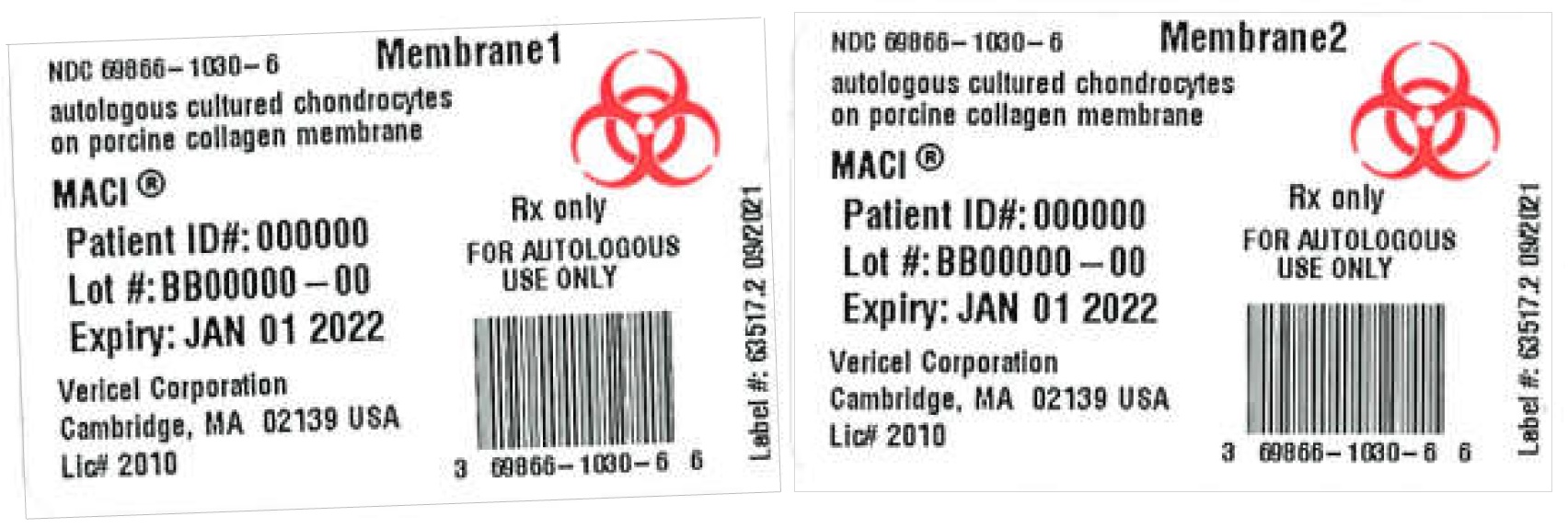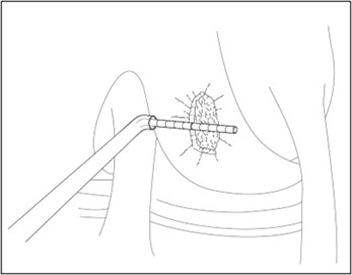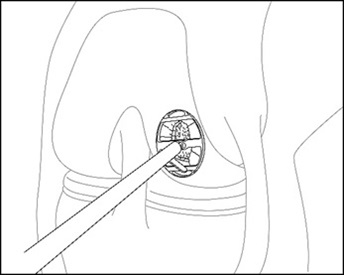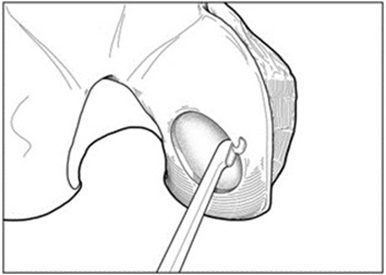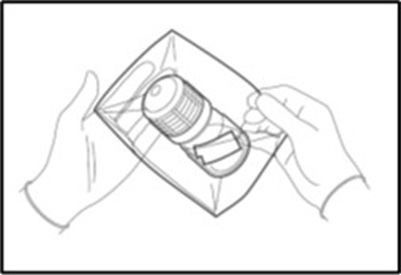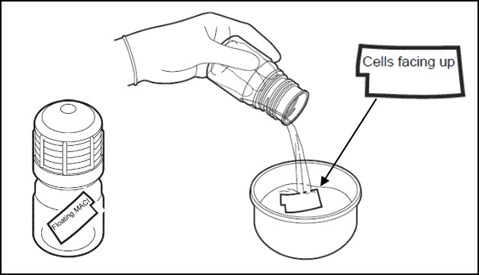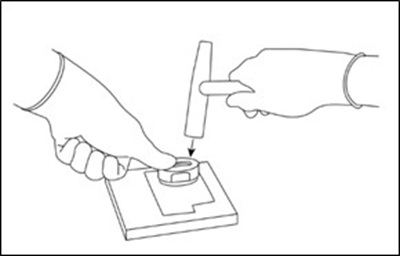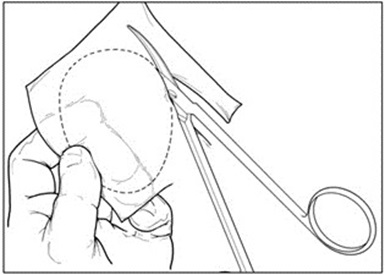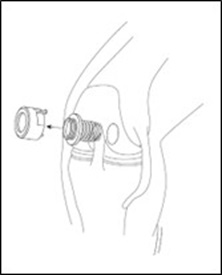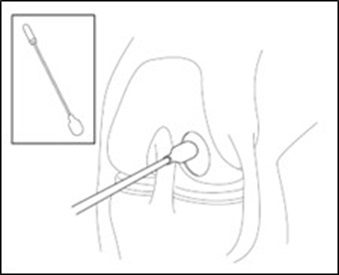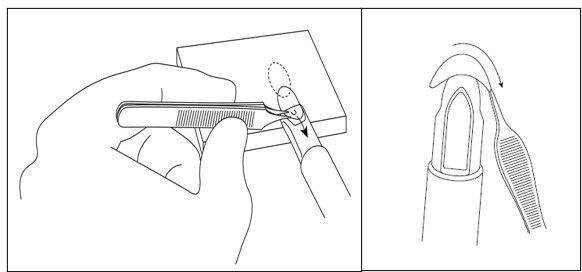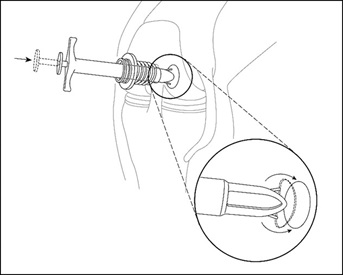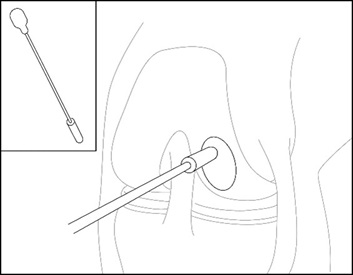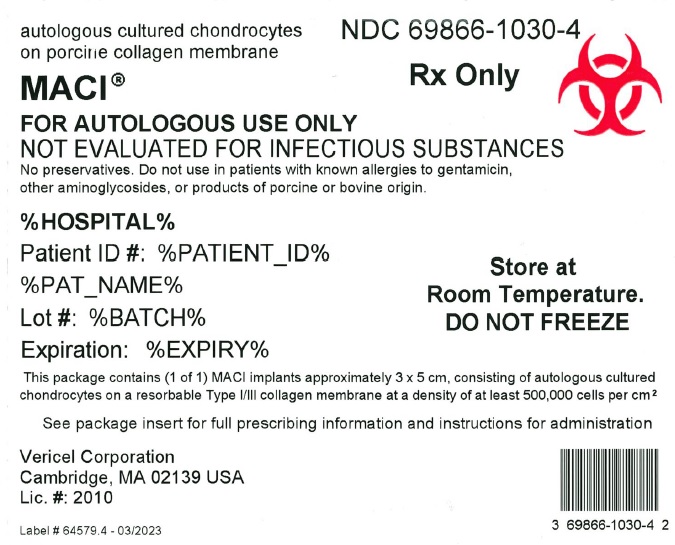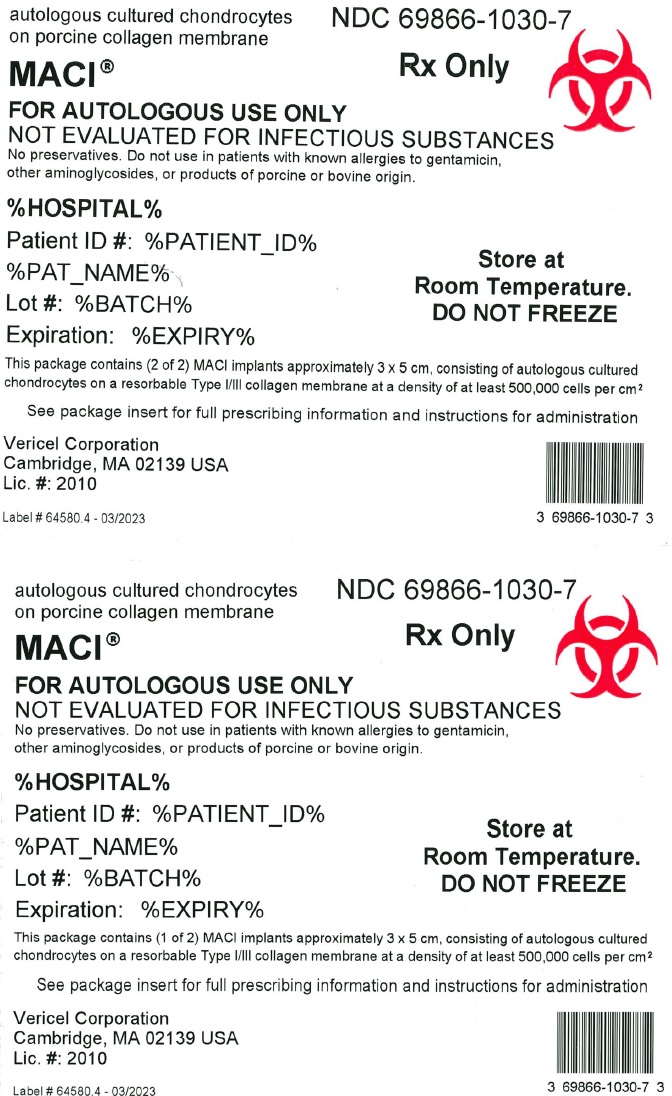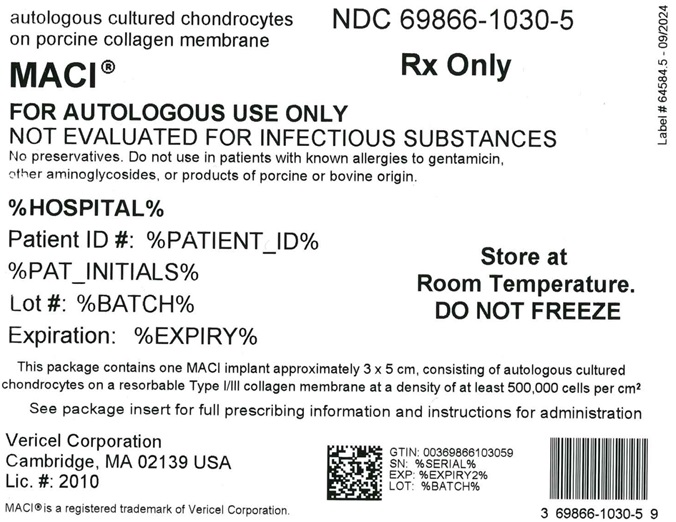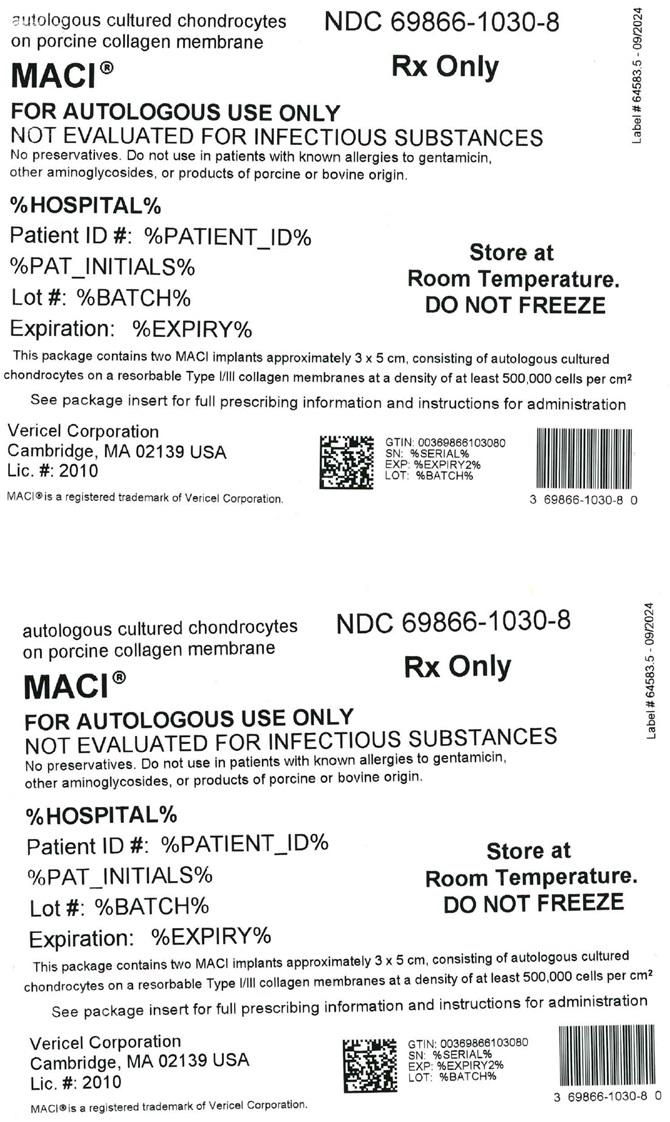 DRUG LABEL: MACI
NDC: 69866-1030 | Form: IMPLANT
Manufacturer: Vericel Corporation
Category: other | Type: CELLULAR THERAPY
Date: 20250918

ACTIVE INGREDIENTS: AUTOLOGOUS CULTURED CHONDROCYTES 15000000 1/1 1; PORK COLLAGEN 15 cm2/1 1

HIGHLIGHTS OF PRESCRIBING INFORMATION

These highlights do not include all the information needed to use MACI safely and effectively. See full prescribing information for MACI.
MACI® (autologous cultured chondrocytes on porcine collagen membrane)
Cellular sheet for autologous implantation
Initial U.S. Approval: 2016

1 INDICATIONS AND USAGE

MACI® is an autologous cellularized scaffold product indicated for the repair of symptomatic, single or multiple full-thickness cartilage defects of the knee with or without bone involvement in adults. (1)

Limitations of Use

- Effectiveness of MACI in joints other than the knee has not been established.
- Safety and effectiveness of MACI in patients over the age of 55 years have not been established.

2 DOSAGE AND ADMINISTRATION

For autologous implantation only.

- Contact Vericel at 1-800-453-6948 or www.MACI.com regarding training materials for surgical implantation of MACI. (2)
- The amount of MACI implanted depends on the size (surface area in cm^2) of the cartilage defect. (2.1)
- MACI should be cut to the size and shape of the defect and implanted with the cell-side down. (2.2)

3 DOSAGE FORMS AND STRENGTHS

Each 3 x 5 cm cellular sheet (MACI implant) consists of autologous cultured chondrocytes on a resorbable porcine Type I/III collagen membrane, at a density of at least 500,000 cells per cm^2. (3)

4 CONTRAINDICATIONS

- Known history of hypersensitivity to gentamicin, other aminoglycosides, or products of porcine or bovine origin. (4)
- Severe osteoarthritis of the knee. (4)
- Inflammatory arthritis, inflammatory joint disease, or uncorrected congenital blood coagulation disorders. (4)
- Prior knee surgery (within 6 months), excluding surgery to procure a biopsy or a concomitant procedure to prepare the knee for a MACI implant. (4)
- Inability to cooperate with a physician-prescribed post-surgical rehabilitation program. (4)

5 WARNINGS AND PRECAUTIONS

- Malignancy: The risk of malignancy in the area of cartilage biopsy or implant is unknown. Expansion of malignant or dysplastic cells present in biopsy tissue during manufacture and subsequent implantation may be possible. (5.1)
- Transmissible infectious diseases: Because patients undergoing procedures associated with MACI are not routinely tested for transmissible infectious diseases, cartilage biopsy and MACI implant may carry risk of transmitting infectious diseases. (5.2)
- Presurgical Comorbidities: Local inflammation or active infection in the bone, joint, and surrounding soft tissue, meniscal pathology, cruciate ligament instability, and misalignment should be assessed and treated prior to or concurrent with MACI implantation. (5.3)
- Product Sterility: Final sterility test results are not available at the time of shipping. (5.4)

6 ADVERSE REACTIONS

The most frequently occurring adverse reactions (≥5%) reported for MACI were arthralgia, tendonitis, back pain, joint swelling, and joint effusion. (6)

Serious adverse reactions reported for MACI were arthralgia, cartilage injury, meniscus injury, treatment failure, and osteoarthritis. (6)

To report SUSPECTED ADVERSE REACTIONS, contact Vericel at 1-800-453-6948 or FDA at 1-800-FDA-1088 or www.fda.gov/medwatch for voluntary reporting of adverse reactions.

8 USE IN SPECIFIC POPULATIONS

Pregnancy: Because MACI implantation requires invasive surgical procedures, use in pregnancy is not recommended. (8.1)

FULL PRESCRIBING INFORMATION

1 INDICATIONS AND USAGE

MACI® (autologous cultured chondrocytes on porcine collagen membrane) is an autologous cellularized scaffold product indicated for the repair of single or multiple symptomatic, full-thickness cartilage defects of the knee with or without bone involvement in adults.

Limitations of Use

- Effectiveness of MACI in joints other than the knee has not been established.
- Safety and effectiveness of MACI in patients over the age of 55 years have not been established.

2 DOSAGE AND ADMINISTRATION

For Autologous Implantation Only.

Contact Vericel at 1-800-453-6948 or www.MACI.com regarding training materials for surgical implantation of MACI.

2.1 Dosage

- The amount of MACI implanted depends on the size (surface area in cm^2) of the cartilage defect. The surgeon should cut the MACI implant to the size and shape of the defect, to ensure the damaged area is completely covered.
- MACI implant is for single-use.
- Multiple implants may be used if there is more than one defect. The size of MACI is adjusted for the size of each cartilage defect.

2.2 Preparation and Implantation Procedure

Collection of Autologous Cartilage Biopsy

- The procedure may be performed arthroscopically.
- Using a ring curette or curved notchplasty gouge, harvest at least two (2) healthy full-thickness cartilage specimens from a lesser load-bearing area of the damaged knee, such as the lateral intercondylar notch, the superior lateral trochlear ridge, or the superior medial trochlear ridge.
- The specimens should measure approximately 5 x 8 mm each (200-300 mg total).
- The biopsy must be full-thickness and should include a small amount of subchondral bone, which will be removed prior to processing the biopsy.
- Some punctate bleeding may occur at the site of biopsy harvest.
- Using sterile technique, place the biopsy into transport medium bottle.

Pre-Operative Preparation

- Confirm that the patient’s identity matches the patient identifiers on the MACI labels.
- Inspect the sealed MACI shipping box for any evidence of damage.
- Open the MACI shipping box and inspect the internal packaging for leaks (liquid) in the outer bag or self-seal pouch containing the bottle holding the MACI implant or for any evidence of damage or contamination.
- DO NOT USE if the patient identifiers do not match, or there are signs of leaking or damage to the packaging. Contact MACI representative immediately or call Vericel Customer Care at 1-800-453-6948.
- After inspection, keep MACI in its original packaging and store at room temperature until the surgical site has been prepared.
- Arthroscopic delivery is for lesions that are a maximum of 4 cm^2 in size and are accessible using an arthroscopic approach.

Implantation Procedure

- Perform implantation procedure during arthrotomy or arthroscopy using sterile surgical techniques.
- Follow the implantation with an appropriate, physician-prescribed rehabilitation program [see Dosage and Administration (2.3)].
- NOTE:
  - The MACI Surgical Implantation Kit may be used to assist with MACI knee surgery via arthrotomy.
  - The MACI Arthroscopic Instruments may be used to assist with arthroscopic delivery.
  - Ensure instruments selected are appropriately matched to the defect size.

Preparing Defect

Arthroscopic Delivery:

- Create an appropriately placed portal to to visualize the defect to be treated athroscopically.
- Under direct arthroscopic vision insert a spinal needle directly over the center of the cartilage defect.
- Use the location determined by the spinal needle to create a second portal for the cannula (e.g., MACI Cannula Assembly) directly perpendicular to the defect.
- Measure the length and width of the defect using a measurement probe (e.g., measurement device) as shown in Figure 1.

Figure 1: Measure defect size – Arthroscopic Method

- Select and insert the appropriate size cannula (e.g., MACI Cannula Assembly) in this second portal directly over the center of the cartilage defect.
- Remove trocar from cannula assembly.
- Select the appropriate size cutter (e.g., MACI Arthroscopic Cutter) based on the defect size.
- Insert the cutter through the cannula and position over the cartilage defect. Adjust the angle of the cutter head, and apply pressure to score the cartilage surrounding the defect (Figure 2). Bring the cutter head back to its original position prior to removal from the joint.

Figure 2: Score Cartilage – Arthroscopic Method

For Arthroscopic and Arthrotomy Delivery:

- For chondral defects, remove all damaged and fibrous tissue on the defect bed using appropriate instruments (e.g., MACI Rake Curette, MACI Square Curette and MACI Open-Ring Curette). Debride the defect bed back to stable cartilage with vertical walls down to the subchondral bone by removing as little healthy cartilage as possible (Figure 3). Do not penetrate the subchondral bone.
  Figure 3: Preparing Defect Bed
- For osteochondral defects, debride the defect bed back to stable cartilage with vertical walls down to healthy stable bone.
- Avoid bleeding through the subchondral plate. If bleeding occurs, use a suitable hemostatic agent to control the bleeding.

Preparing MACI Implant

- Unpacking MACI implant box (outside sterile field).
  - Unpack MACI implant shipping box.
  - Staff responsible for removing bottle from packaging and decanting contents into sterile container in sterile field should wear protective gown, gloves, and eyewear.
  - Remove the outer bag containing a bottle holding the MACI implant.
  - Remove the self-seal pouch containing the bottle from the outer bag (Figure 4).
    Figure 4: Bottle in Self-Sealed Pouch
  - Tear notches on the self-seal pouch to open the pouch and remove the bottle.
    Note: Keep the bottle upright and do not open the cap until ready to use the MACI implant.
    Note: Do not remove the MACI implant from the bottle until ready to be used.
- Unpacking the MACI implant bottle (Figure 5)
  - When ready, a team member outside the sterile field but adjacent to the sterile prep table, will twist open and remove the cap from the bottle. The outside of the bottle is not sterile, ensure that the MACI implant or sterile instruments do not come in contact with the outside of the bottle.
  - On sterile field, place sterile dish or container of sufficient size to hold contents of MACI implant bottle, approximately 120 mL of media.
  - Ensure MACI implant is free floating and not adhered to inner surface of bottle.
    Aseptically and rapidly decant the bottle contents into sterile dish including all transport media and the MACI implant.
    Note: If the MACI implant remains in the bottle, media from the sterile dish can be returned to the bottle via sterile syringe and decanted again. Alternatively, if the MACI has remained in the neck of the bottle, it can be extracted using sterile non-toothed forceps to grasp an edge or corner.
    Figure 5: Unpacking MACI Implant
  - The MACI implant has a rough side and a smooth side. The cells are seeded on the rough side. A notch in the lower left corner of the implant in landscape orientation indicates that the cell-side is facing up.
  - The cell-side of the MACI implant should remain facing up at all times until placement into the defect. If the MACI implant is cell-side down after decanting from bottle, a sterile field team member will flip the membrane using two (2) sterile non-toothed forceps. The MACI implant should only be grasped by corners or edges.
  - Sterile field team member will use two (2) sterile non-toothed forceps to grasp the MACI implant corners and place the MACI implant cell-side up onto a sterile work surface (e.g., MACI Cutting Block or MACI Arthroscopic Cutting Block). A notch in the lower left corner of the implant indicates that the cell-side is facing up.

Note: The MACI implant must remain hydrated with the shipping media.
Use the decanted media from the sterile dish to maintain implant hydration after removal from the bottle.

Shaping the MACI implant

- Avoid excessive manipulation of the MACI implant. Throughout the shaping and delivery of the MACI implant it is important to keep track of membrane orientation to facilitate placing cells in the base of the defect.

Arthroscopic Delivery:

- Using the MACI Cutter that was packaged together with the Arthroscopic Cutter, place the MACI Cutter on top of the MACI implant and use light thumb pressure or lightly tap with a mallet to cut to size (Figure 6).
  Figure 6: Cut MACI Implant
- Place any remaining MACI implant into a separate intermediary dish with adequate media to keep the implant hydrated.

Arthrotomy Delivery:

- Create an exact template of the defect (Figure 7).
  Figure 7: Creating Defect Template
- Create orientation markers on the template to assist with proper orientation of the MACI implant. Turn the marked template over to ensure that the cells will be properly placed into the defect.
- To maintain proper orientation, turn the template over and place it underneath the MACI implant, against the smooth, non-seeded side. The template should be visible through the translucent implant.
  Note: Ensure minimal contact with the cell-seeded surface of the MACI implant.
- Using the template as a guide, cut the MACI implant to the correct size and shape.
- Place the custom-cut implant into a sterile intermediary dish, ensuring the cell-side up orientation. Ensure MACI implant remains hydrated at all times. Using sterile syringe, hydrate implant using decanted media.
- Place any remaining MACI implant into a separate intermediary dish with adequate media to keep the implant hydrated.

Placing MACI Implant

Arthroscopic Delivery

- Turn off fluid and drain the knee.
- If using a cannula with a dam (e.g., MACI Arthroscopic instrument), remove the dam from the cannula (Figure 8). Do not insert the MACI implant through a cannula dam.
  Figure 8: Remove Cannula Dam
- A dry arthroscopic environment is essential for implantation. Remove any close liquid collections with the suction tip and ensure the defect area is dry and free of bleeding (e.g., using the spongy end of the MACI Applicator) (Figure 9).
  Figure 9: Dry Defect
- Select appropriate size MACI V-Shuttle Delivery Device that matches the MACI Cannula diameter size used.
- Verify the V-Shuttle delivery device functionality by pressing the plunger to deploy the antennae prior to use.
- Gently place the MACI implant cell-side (rough side) up on the tip of the MACI V-Shuttle delivery device using forceps (Figure 10). Maintain the orientation of the V-Shuttle in an upright position.
  Figure 10: Placement on MACI V-Shuttle Delivery Device
- Apply a thin layer of fibrin sealant to the entire base of the defect (bone) bed.
- Insert the MACI V-Shuttle with the loaded MACI implant into the MACI cannula ensuring the outer fins of the V Shuttle are oriented inferior and superior in line with the lesion. Slowly slide V-Shuttle through the cannula until the implant is positioned just over the defect.
- Once the MACI implant and MACI V-Shuttle are properly positioned directly over the center of the defect, gently push the plunger on the V-Shuttle to deploy the antennae to deliver the implant into the defect (Figure 11).
  Note: Do not compress the implant between the bone and the tip of the V-Shuttle. This may damage the cells on the MACI implant.
- Once the MACI implant is delivered into the defect, depress the plunger to retract the antennae and slowly retract the V-Shuttle from the cannula.
  Figure 11: Arthroscopic Delivery of MACI Implant to Defect
- Gently adjust placement of the MACI implant to desired location using a tamp (e.g., the silicone end of the MACI Applicator) and allow at least 3 minutes for the sealant to set (Figure 12).
  Figure 12: Placement of the MACI Implant
- Assess that the fibrin sealant has set and the MACI implant has adhered through the following methods: gently probing the implant with a blunt instrument (e.g. MACI Applicator), and repeated cycles of flexion and extenson of the knee.

Arthrotomy Delivery:

- Ensure defect area is dry and free of bleeding.
- Apply a thin layer of fibrin sealant to the entire base of the defect (bone) bed.
- Maintaining appropriate rotational orientation, place the custom-cut implant onto the defect bed cell-side down.
- Apply light digital pressure to the implant for approximately 3 minutes to allow sealant to set.
- Assess that the fibrin sealant has set and the MACI implant has adhered through the following methods: gently probing the implant with a blunt instrument (e.g. MACI Applicator), and repeated cycles of flexion and extension of the knee.
- MACI implant fixation may also be supplemented with interrupted resorbable sutures if desired or if conditions warrant, particularly if the defect is uncontained (i.e, the cartilage defect is not 100% surrounded by a stable cartilage rim) or the lesion is larger than 10 cm^2.

For Arthroscopic and Arthrotomy Delivery:

- Fibrin sealant may also be applied to the rim (periphery) of the implant.
- Discard unused MACI implant and media using bio-hazard hospital protocols.

2.3 Postsurgical Rehabilitation

A physician-prescribed rehabilitation program that includes early mobilization, joint range of motion, and weight bearing is recommended to promote graft maturation and reduce the risk of graft delamination, postoperative thromboembolic events, and joint stiffness. Stage this program to promote a progressive return to full joint range of motion and weight-bearing as well as muscle strengthening and conditioning. Return to recreational and sporting activity should be in consultation with healthcare professionals.

3 DOSAGE FORMS AND STRENGTHS

MACI implant is available as a cellular sheet, 3 x 5 cm, with a 0.5-cm^2 section removed from the lower left-hand corner, consisting of autologous cultured chondrocytes on a resorbable Type I/III collagen membrane at a density of at least 500,000 cells per cm^2.

4 CONTRAINDICATIONS

MACI is contraindicated in patients with the following conditions:

- Known history of hypersensitivity to gentamicin, other aminoglycosides, or products of porcine or bovine origin. [see Description (11)]
- Severe osteoarthritis of the knee (Kellgren-Lawrence grade 3 or 4).
- Inflammatory arthritis, inflammatory joint disease, or uncorrected congenital blood coagulation disorders.
- Prior knee surgery (6 months), excluding surgery to procure a biopsy or a concomitant procedure to prepare the knee for a MACI implant.
- Inability to cooperate with a physician-prescribed post-surgical rehabilitation program [See Dosage and Administration (2.3)].

5 WARNINGS AND PRECAUTIONS

5.1 Malignancy

The safety of MACI used in patients with malignancy in the area of cartilage biopsy or implant is unknown. The potential exists for expansion of malignant or dysplastic cells present in biopsy tissue during manufacture and subsequent implantation. In addition, implantation of normal autologous chondrocytes could theoretically stimulate growth of malignant cells in the area of the implant, although there have been no such incidents reported in humans or animals.

5.2 Transmissible Infectious Diseases

MACI is intended solely for autologous use. Patients undergoing the surgical procedures associated with MACI are not routinely tested for transmissible infectious diseases. Therefore, the cartilage biopsy and the MACI implant may carry the risk of transmitting infectious diseases to personnel handling these tissues. Accordingly, healthcare providers should employ universal precautions in handling the biopsy samples and the MACI product.

Product manufacture includes reagents derived from animal materials. All animal-derived reagents are tested for viruses, retroviruses, bacteria, fungi, yeast, and mycoplasma before use. Bovine materials are sourced to minimize the risk of transmitting a prion protein that causes bovine spongiform encephalopathy and may cause a rare fatal condition in humans called variant Creutzfeldt-Jakob disease.

These measures do not totally eliminate the risk of transmitting these or other transmissible infectious diseases and disease agents. Report the occurrence of a transmitted infection to Vericel Corporation at 1-800-453-6948.

5.3 Presurgical Assessment of Comorbidities

To create a favorable environment for healing, assess and treat the following conditions prior to or concurrent with implantation with MACI:

- Local inflammation or active infection in the bone, joint, and surrounding soft tissue: patients should be deferred until complete recovery.
- Meniscal pathology: presence of an unstable or torn meniscus requires partial resection, repair, or replacement prior to or concurrent with MACI implantation. MACI is not recommended in patients with a total meniscectomy.
- Cruciate ligament instability: the joint should not possess excessive laxity, which may create excessive shear and rotational forces across the joint. Both anterior and posterior cruciate ligaments should be stable or undergo reconstruction prior to or concurrent with MACI implantation.
- Misalignment: the tibio-femoral joint should be properly aligned, and patella tracking should be normalized. Varus or valgus misalignment of the tibio-femoral joint and abnormal patella tracking may abnormally load joint surfaces and jeopardize the implant. Misalignment and patella tracking should be addressed with a corrective osteotomy or similar corrective procedure prior to or concurrent with MACI implantation.

5.4 Product Sterility

MACI is shipped after passing preliminary test results from in-process microbial tests. A final sterility test is initiated prior to shipping, but the result will not be available prior to implantation. If microbial contamination is detected after the product has been shipped, Vericel will notify the healthcare provider(s) and recommend appropriate actions.

6 ADVERSE REACTIONS

The most frequently occurring adverse reactions (≥5%) reported for MACI were arthralgia, tendonitis, back pain, joint swelling, and joint effusion.

Serious adverse reactions reported for MACI were arthralgia, cartilage injury, meniscus injury, treatment failure, and osteoarthritis.

6.1 Clinical Trials Experience

Because clinical trials are conducted under widely varying conditions, adverse reaction rates observed in the clinical trials of a product cannot be directly compared to rates in the clinical trials of another product and may not reflect the rates observed in practice.

In a 2-year prospective, multicenter, randomized, open-label, parallel-group clinical trial, 144 patients, ages 18 to 54 years, were randomized to receive a 1-time treatment with MACI or microfracture (1:1, 72 patients in each treatment group). Demographic characteristics of patients in the trial were similar in both treatment groups. The majority of patients were male (62.5% MACI, 66.7% microfracture), and the mean ages were 34.8 (MACI) and 32.9 (microfracture) years. Overall, 70 patients in the MACI group and 67 patients in the microfracture group completed 2 years of follow-up.

In addition, all 144 subjects from the 2-year clinical trial had the option to enroll in a 3-year follow-up study (extension study). Safety and efficacy assessments were performed at yearly scheduled visits. The demographic characteristics of patients (N = 128) enrolled in the extension study were similar in both treatment groups and consistent with the overall population of the 2-year clinical trial.

The proportion of patients with at least one (1) subsequent surgical procedure (any surgical procedure performed on the treated knee joint, including arthroscopy, arthrotomy, or manipulation under anesthesia) in the 2 years following study treatment was comparable between treatment groups (8.3% in the MACI group and 9.7% in the microfracture group).

Adverse reactions reported in ≥5% of patients in either treatment group in the 2-year clinical trial are provided in Table 1.

Table 1. Adverse Reactions in ≥5% of Patients in Any Treatment Group in the 2-Year Clinical Trial
System Organ Class | MACI n = 72 n (%) | Microfracture n = 72 n (%)
Musculoskeletal and Connective Tissue Disorders
Arthralgia | 37 (51.4) | 46 (63.9)
Back pain | 8 (11.1) | 7 (9.7)
Joint swelling | 7 (9.7) | 4 (5.6)
Joint effusion | 5 (6.9) | 4 (5.6)
Injury, Poisoning and Procedural Complications
Cartilage injury | 3 (4.2) | 9 (12.5)
Ligament sprain | 3 (4.2) | 5 (6.9)
Procedural pain | 3 (4.2) | 4 (5.6)
General Disorders and Administration Site Conditions
Treatment failure | 1 (1.4) | 4 (5.6)

In the 3-year extension study, adverse reactions reported in ≥5% of patients were (MACI vs microfracture): arthralgia (46.2% vs 50.8%), tendonitis (6.2% vs 1.6%), back pain (4.6% vs 6.3%), osteoarthritis (4.6% vs 7.9%), joint effusion (3.1% vs 7.9%), cartilage injury (6.2% vs 15.9%), procedural pain (3.1% vs 7.9%), ligament sprain (1.5% vs 7.9%), and treatment failure (4.6% vs 7.9%).

Serious adverse reactions reported in patients in either treatment group for integrated data across the 2-year clinical trial and the 3-year extension study are provided in Table 2.

Table 2. Serious Adverse Reactions in Patients in Any Treatment Group Across the 2-Year Clinical Trial and the 3-Year Extension Study
System Organ Class | MACI n = 72 n (%) | Microfracture n = 72 n (%)
Musculoskeletal and Connective Tissue Disorders
Arthralgia | 1 (1.4) | 7 (9.7)
Back pain | 0 | 3 (4.2)
Joint swelling | 3 (4.2) | 0
Joint effusion | 3 (4.2) | 0
Injury, Poisoning and Procedural Complications
Cartilage injury | 3 (4.2) | 8 (11.1)
General Disorders and Administration Site Conditions
Treatment failure | 3 (4.2) | 7 (9.7)

6.2 Postmarketing Experience

Graft complication (e.g., abnormalities to the repair graft that become symptomatic; this could include graft overgrowth [tissue hypertrophy], under-fill or damage to the repair tissue that has elicited a painful response, or mechanical symptoms), graft delamination (i.e., a dislodging of the repair graft from the underlying subchondral bone that has become symptomatic; this can be measured as marginal, partial, or a complete delaminated graft), and tendonitis have been reported during use of MACI outside the United States. Because these reactions are reported voluntarily from a population of uncertain size, it is not always possible to reliably estimate their frequency or establish a causal relationship to MACI exposure.

8 USE IN SPECIFIC POPULATIONS

8.1 Pregnancy

Risk Summary

MACI implantation requires invasive surgical procedures; therefore use during pregnancy is not recommended. Limited clinical data on patients exposed to MACI during pregnancy are available. There are insufficient data with MACI use in pregnant women to inform a product-associated risk. Animal reproduction studies have not been conducted with MACI. In the U.S. general population, the estimated background risk of major birth defects and miscarriage in clinically recognized pregnancies is 2-4% and 15-20%, respectively.

8.2 Lactation

Risk Summary

There is no information regarding the presence of MACI in human milk, the effects on the breastfed infant, or the effects on milk production. The developmental and health benefits of breastfeeding should be considered along with the mother’s clinical need for MACI and any potential adverse effects on the breastfed infant from MACI or from the underlying maternal condition.

8.4 Pediatric Use

The safety and effectiveness of MACI in pediatric patients have not been established.

8.5 Geriatric Use

The safety and effectiveness of MACI in patients over 65 years of age have not been established. Clinical trials of MACI did not include subjects over the age of 55.

11 DESCRIPTION

MACI, autologous cultured chondrocytes on porcine collagen membrane, is a cellular sheet that consists of autologous chondrocytes seeded on a 3 x 5 cm, resorbable porcine Type I/III collagen membrane, for implantation into cartilage defects of the knee. The active ingredients of MACI are the autologous cultured chondrocytes and porcine Type I/III collagen. The autologous chondrocytes are propagated in cell culture and are seeded on the collagen at a density of 500,000 to 1,000,000 cells per cm^2. The final MACI implant contains at least 500,000 cells per cm^2 and does not contain any preservative.

The product manufacture also uses reagents derived from animal materials. The resorbable, Type I/III, collagen membrane, which is a component of MACI, is porcine-derived. Fetal bovine serum is a component in the culture medium used to propagate the autologous chondrocytes; therefore, trace quantities of bovine-derived proteins may be present in MACI. These animal-derived reagents are tested for viruses, retroviruses, bacteria, fungi, yeast, and mycoplasma before use.

MACI may contain residual gentamicin because it is included during manufacture. Gentamicin is not included in the transport medium used to maintain product stability. Studies determined an average of 9.2 μg residual gentamicin per MACI implant.

A final sterility test is initiated prior to shipping, but the result will not be available prior to implantation. Passing results from preliminary in-process microbial tests are required for release of MACI for shipping.

12 CLINICAL PHARMACOLOGY

12.1 Mechanism of Action

No clinical pharmacology studies have been conducted with MACI and a mechanism of action has not been established.

12.3 Pharmacokinetics

Clinical pharmacokinetic studies have not been performed with MACI. Studies in rabbits and horses indicated that the membrane is resorbed over a period of at least 6 months following implantation.

13 NONCLINICAL TOXICOLOGY

13.1 Carcinogenesis, Mutagenesis, Impairment of Fertility

Studies to evaluate the carcinogenicity or impairment of fertility potential of MACI have not been performed. In vitro studies have shown that the expansion process for chondrocytes does not induce changes to the cellular karyotype.

Four studies (in vitro and in vivo) were conducted to assess the genotoxic potential of the collagen membrane. The results from these studies demonstrated that the collagen membrane was non-mutagenic.

13.2 Animal Toxicology and/or Pharmacology

Implantation of analogous products in critical-size defects in the hind limbs of rabbits and horses did not reveal any serious safety concerns. The products consisted of the same membrane as MACI with rabbit or horse cells, respectively. Non-clinical testing has shown that the collagen membrane is not toxic and is compatible with biological tissue.

14 CLINICAL STUDIES

The effectiveness of MACI implant was evaluated in a 2-year prospective, multicenter, randomized, open-label, parallel-group study, SUMMIT (Superiority of MACI implant versus Microfracture Treatment in patients with symptomatic articular cartilage defects in the knee), which enrolled a total of 144 subjects, ages 18 to 54 years, with at least one symptomatic Outerbridge Grade III or IV focal cartilage defect on the medial femoral condyle, lateral femoral condyle, and/or the trochlea. Failure of a prior cartilage surgery was not required for study entry. The subjects were randomized to receive either a 1-time treatment with MACI or microfracture. The co-primary efficacy endpoint was change from baseline to Week 104 for the subject’s Knee injury and Osteoarthritis Outcome Score (KOOS) in two subscales: Pain and Function (Sports and Recreational Activities [SRA])¹. Safety also was evaluated through Week 104 [see Adverse Reactions (6.1)].

Of the 72 subjects randomized to MACI, 70 completed the study and two (2) discontinued prematurely (one (1) due to an adverse event [AE] and one (1) wished to withdraw). Of the 72 subjects randomized to microfracture, 67 completed the study and five (5) discontinued prematurely (one (1) due to an AE, one (1) wished to withdraw, and three (3) due to lack of clinical benefit).

At Week 104, KOOS pain and function (SRA) had improved from baseline in both treatment groups, but the improvement was statistically significantly (p = 0.001) greater in the MACI group compared with the microfracture group (Table 3).

Table 3. Change in KOOS Pain and Function (SRA) Scores in the 2-Year Study
 | MACI Mean (SD) |  |  | Microfracture Mean (SD)
 | N | Pain | Function | N | Pain | Function
Baseline | 72 | 37.0 (13.5) | 14.9 (14.7) | 71 | 35.4 (12.1) | 12.6 (16.7)
Week 104 | 72 | 82.4 (16.2) | 60.9 (27.8) | 70 | 70.9 (24.2) | 48.7 (30.3)
Change From Baseline to Week 104 | 72 | 45.4 (21.1) | 46.0 (28.4) | 69 | 35.2 (23.9) | 35.8 (31.6)
LS Means (Week 104) |  | 44.1 | 46.1 |  | 32.4 | 34.6
Difference [Difference in least squares mean values at Week 104 [MACI – Microfracture].] [MACI – Microfracture] |  | 11.8 | 11.4
p-value [p-value for difference in co-primary endpoints assessed jointly at Week 104 based on multivariate analysis of variance.] | 0.001
LS = least squares; KOOS = Knee injury and Osteoarthritis Outcome Score; SD = standard deviation; SRA = Sports and Recreational Activities.

In a responder analysis, the proportion of subjects with at least a 10-point improvement in both KOOS pain and function (SRA) was greater in the MACI group (63/72=87.5%; 95% CI [77.6%, 94.1%]) compared with the microfracture group (49/72=68.1%; 95% CI [56.0%, 78.6%]).

All subjects from the 2-year study had the option to enroll in a 3-year follow-up study (extension study), in which 128 subjects participated. All 65 subjects (100%, 65/65) in the MACI group and 59 subjects (93.7%, 59/63) in the microfracture group completed the extension study. The mean 2-year KOOS pain and function scores remained stable for the additional 3-year period in both treatment groups (Table 4).

Table 4. KOOS Pain and Function (SRA) Scores in the 3-Year Extension Study
Visit | MACI |  |  | Microfracture
Visit | N | Pain mean (SD) | Function mean (SD) | N | Pain mean (SD) | Function mean (SD)
Baseline | 65/65 | 37.1 (13.1) | 15.4 (14.8) | 63/63 | 35.2 (12.3) | 11.9 (16.2)
2 Years | 63/63 | 82.2 (15.8) | 60.5 (26.5) | 60/60 | 71.8 (23.9) | 48.9 (30.6)
5 Years | 65/64 | 82.2 (20.1) | 61.9 (30.9) | 59/59 | 74.8 (21.7) | 50.3 (32.3)

15 REFERENCES

1. Roos EM, Lohmander LS. The Knee injury and Osteoarthritis Outcome Score (KOOS): from joint injury to osteoarthritis. Health Qual Life Outcomes. 2003;1:64.

16 HOW SUPPLIED/STORAGE AND HANDLING

How Supplied

- A single patient order may contain one (1) or two (2) implants, each in its own bottle and shipper, depending on lesion size and number of lesions.
  MACI - One (1) Implant
- MACI, NDC69866-1030-5 (outer box), contains one (1) implant supplied ready for use as a single cellular sheet approximately 3 x 5 cm, in a sterile, sealed, translucent perfluoroalkoxy (PFA) resin bottle and cap. Each bottle contains one 3 x 5 cm implant with a 0.5-cm^2 section removed from the lower left-hand corner.
  MACI - Two (2) Implant
- MACI, NDC69866-1030-8 (outer box), contains two (2) implants supplied ready for use as cellular sheets approximately 3 x 5 cm, in a sterile, sealed, translucent perfluoroalkoxy (PFA) resin bottle and cap. Each bottle contains one 3 x 5 cm implant with a 0.5 cm^2 section removed from the lower left-hand corner.
- Each bottle is individually sealed in a clear self-seal pouch. Each self-seal pouch is placed into a 95kPa outer bag with absorbent material. These bags are enclosed in an outer box insulated with ambient temperature gel packs.

Storage and Handling

- Store MACI at room temperature in its original packaging (outer box) until ready to use.
- DO NOT REFRIGERATE or FREEZE, or sterilize MACI.
- DO NOT USE if the bottle is damaged, has been compromised, or has leaked.
- Use MACI prior to 11:59 PM EST on the date of expiration printed on the package.
- Dispose of unused MACI or waste material as surgical biohazardous waste in accordance with local requirements.

17 PATIENT COUNSELING INFORMATION

- Advise the patient that:
  - A cartilage biopsy is needed to manufacture MACI. The biopsy is typically performed as an arthroscopic procedure at the time of diagnosis confirmation.
  - The length of time between the biopsy and the implantation of MACI may vary depending on many factors, including the quality and number of cells obtained from the biopsy. Cells can be held in storage until a convenient date for surgery is agreed upon between the patient and the surgeon.
  - Even if the surgeon has taken a biopsy needed to produce MACI, it may be possible that the patient cannot be treated with MACI, (e.g., in case the biopsy is of insufficient quality to produce MACI, if the cells cannot be grown in the laboratory, or if the expanded cells do not meet all the quality requirements).
- Advise the patient on the risk of graft complications, subsequent surgical procedures, and treatment failure. [See Adverse Reactions (6)]
- Advise the patient on general complications related to knee surgery, which may include deep vein thrombosis and pulmonary embolism.
- Advise the patient to closely follow the physician-prescribed rehabilitation program, which will include limitations and allowances for beginning specific physical activities. [See Dosage and Administration (2.3)]
- Inform patient about the possible risk of transmission of infectious diseases with MACI implantation. [See Warnings and Precautions (5.2)]

Manufactured by: Vericel Corporation, 64 Sidney Street, Cambridge, MA 02139
MACI® is a registered trademark of Vericel Corporation.
Patents: www.vcel.com/research-and-development
© 2025 Vericel Corporation.
65628 Revision 4
09/2025